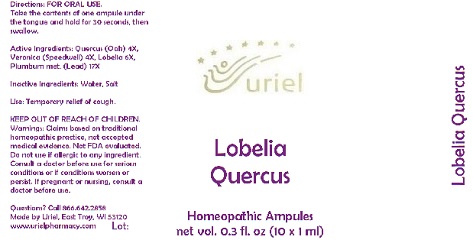 DRUG LABEL: Lobelia Quercus
NDC: 48951-6045 | Form: LIQUID
Manufacturer: Uriel Pharmacy Inc.
Category: homeopathic | Type: HUMAN OTC DRUG LABEL
Date: 20180530

ACTIVE INGREDIENTS: QUERCUS ROBUR WHOLE 4 [hp_X]/1 mL; VERONICA OFFICINALIS FLOWERING TOP 4 [hp_X]/1 mL; LOBELIA SPICATA LEAF 6 [hp_X]/1 mL; LEAD 17 [hp_X]/1 mL
INACTIVE INGREDIENTS: WATER; SODIUM CHLORIDE

Lobelia Quercus

INDICATIONS AND USAGE

Directions: FOR ORAL USE.

DOSAGE AND ADMINISTRATION

Take the contents of one ampule under the tongue and hold for 30 seconds, then swallow.

ACTIVE INGREDIENT

Active Ingredients: Quercus (Oak) 4X, Veronica (Speedwell) 4X, Lobelia 6X, Plumbum met. (Lead) 17X

Inactive Ingredients: Water, Salt

PURPOSE

Use: Temporary relief of cough.

KEEP OUT OF REACH OF CHILDREN.

WARNINGS

Warnings: Claims based on traditional homeopathic practice, not accepted medical evidence. Not FDA evaluated. Do not use if allergic to any ingredient. Consult a doctor before use for serious conditions or if conditions worsen or persist. If pregnant or nursing, consult a doctor before use.

QUESTIONS

Questions? Call 866.642.2858 Made by Uriel, East Troy, WI 53120 www.urielpharmacy.com